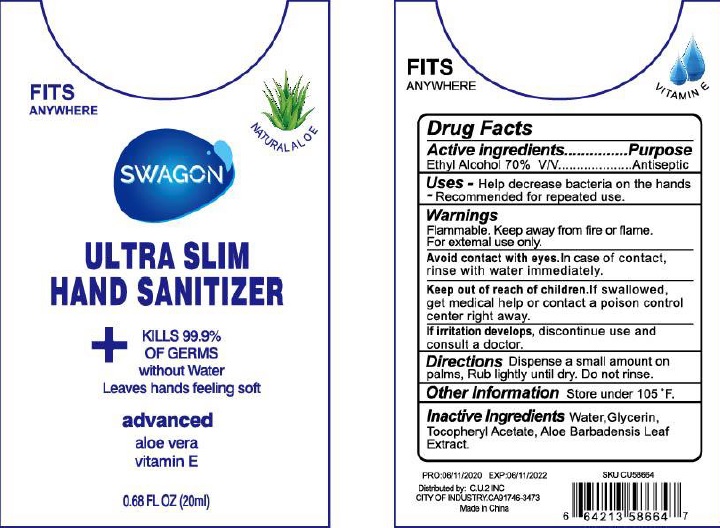 DRUG LABEL: swagon ultra slim hand sanitizer
NDC: 72285-060 | Form: GEL
Manufacturer: Yozzi Co.,ltd
Category: otc | Type: HUMAN OTC DRUG LABEL
Date: 20200808

ACTIVE INGREDIENTS: ALCOHOL 70 mL/100 mL
INACTIVE INGREDIENTS: WATER; GLYCERIN; PROPYLENE GLYCOL; ALOE VERA LEAF; .ALPHA.-TOCOPHEROL ACETATE

HAND SANITIZER

Active Ingredients

Ethyl Alcohol 70% v/v

Purpose

Antiseptic

Use:

- To help reduce bacteria on the skin.
- Recommended for repeated use.

WARNINGS:

For external use only

Flammable. Keep away from fire or flame.

When using this product:

• Keep out of eyes. • In case of contact with eyes, flush thoroughly with water.

If irritation develops, discontinue use and consult a doctor.

Keep out of reach of children.

if swallowed, get medical help or contact a Poison Control Center right away.

Directions:

Dispense a small amount on palms, rub lightly until dry. Do not rinse.

Other Information:

• Store under 105° F

Inactive Ingredients:

Water, Glycerin, Tocopheryl Acetate, Aloe Barbadensis Leaf Extract